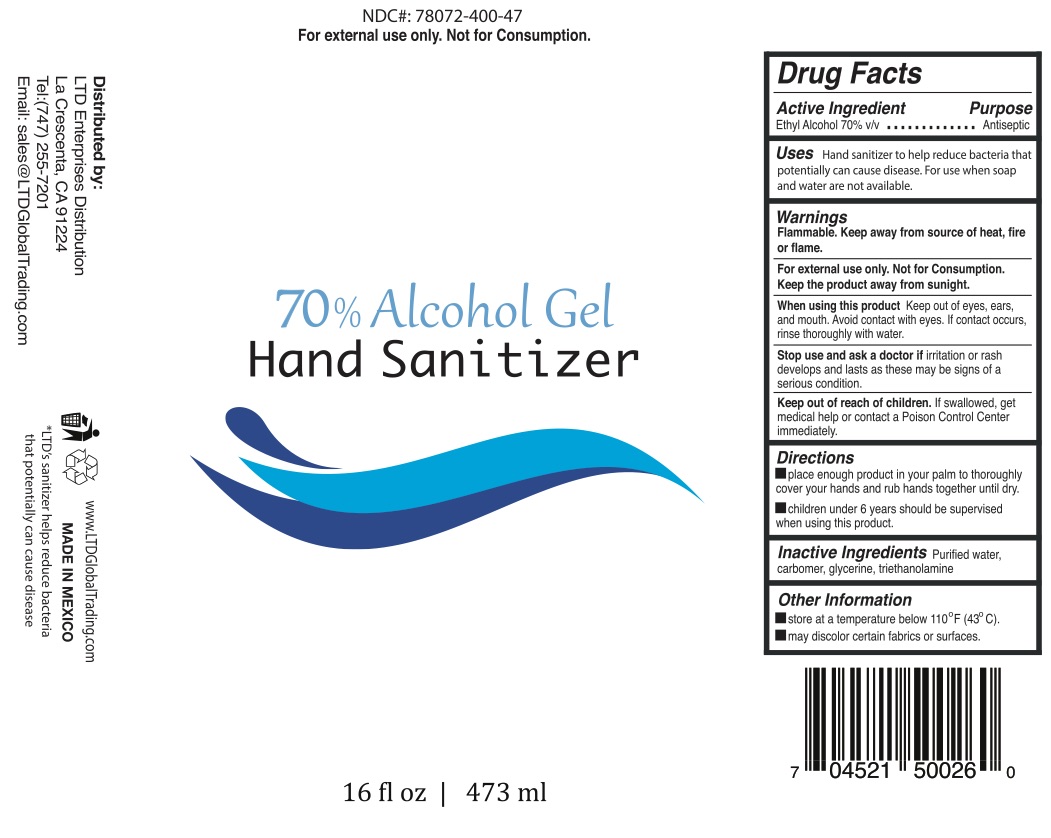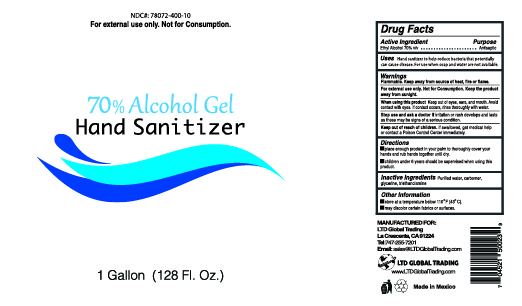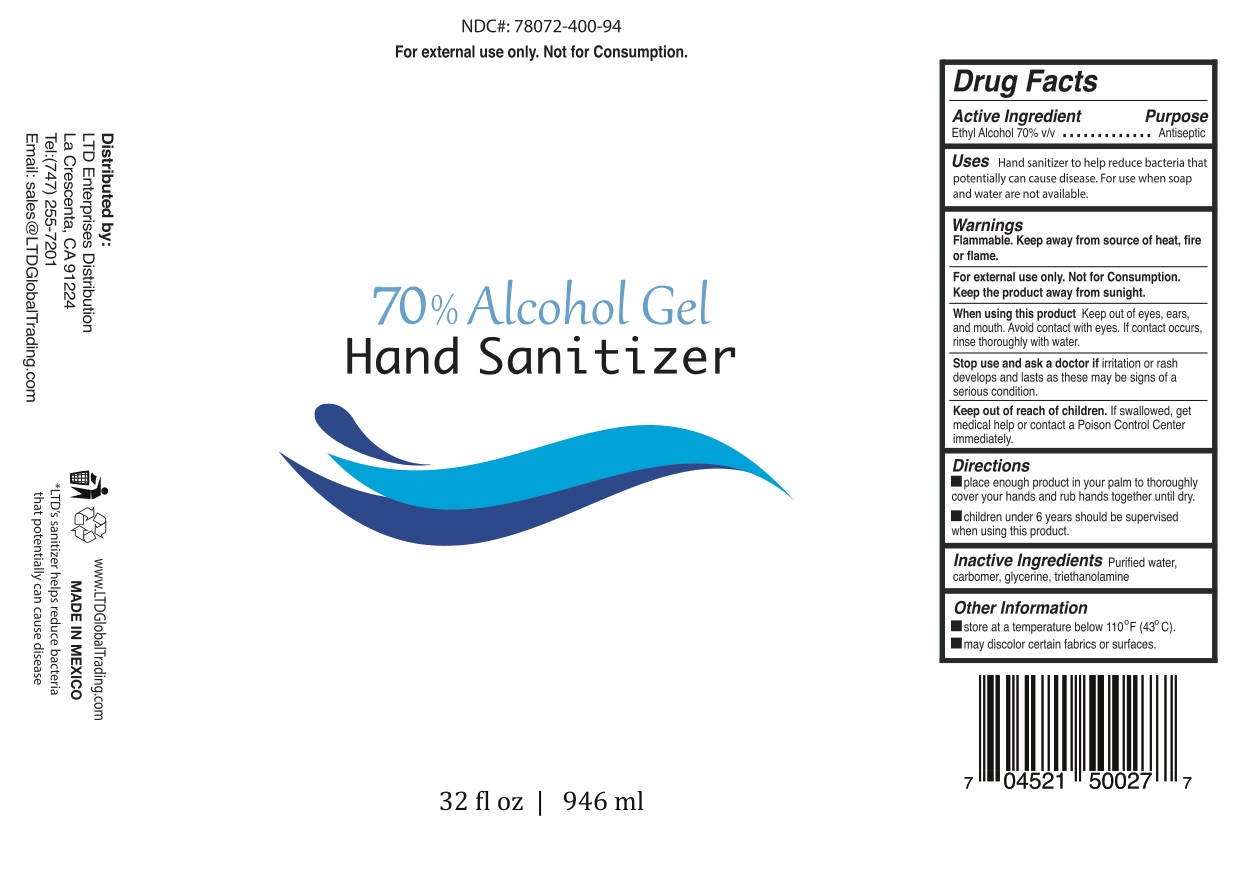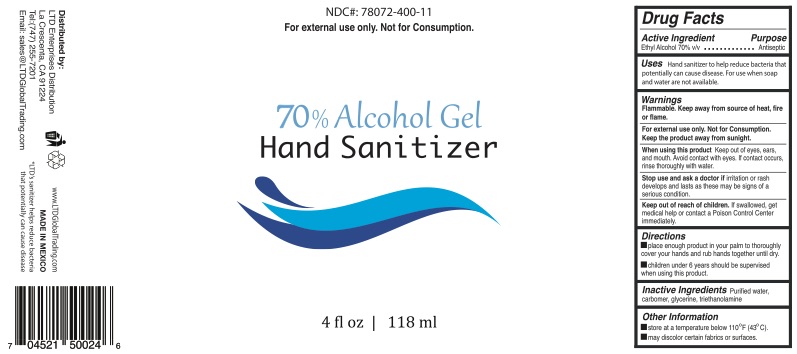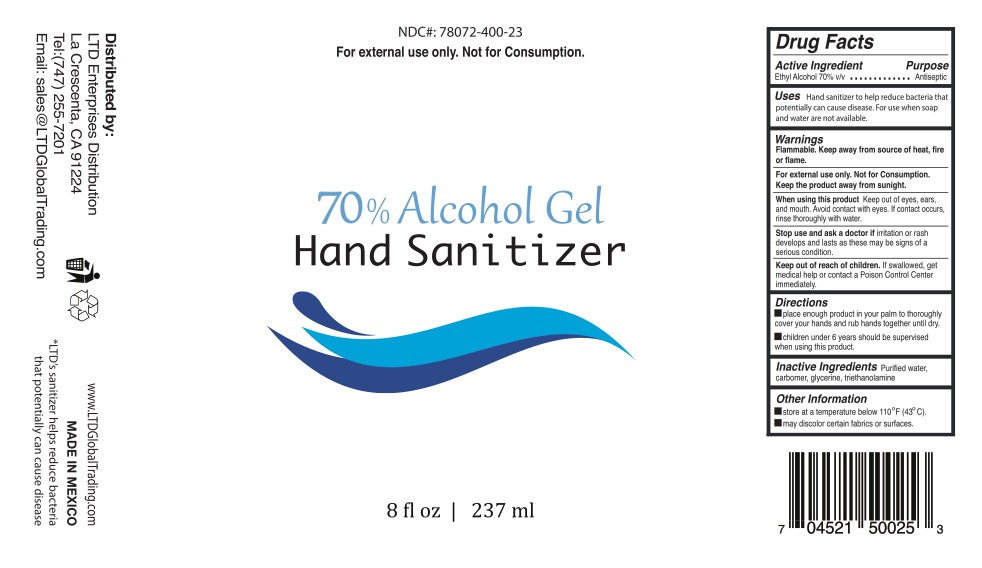 DRUG LABEL: LTD Global Trading 70% Alcohol Hand Sanitizer
NDC: 78072-400 | Form: GEL
Manufacturer: LTD ENTERPRISES DISTRIBUTION, INC.
Category: otc | Type: HUMAN OTC DRUG LABEL
Date: 20200715

ACTIVE INGREDIENTS: ALCOHOL 70 mL/100 mL
INACTIVE INGREDIENTS: WATER; CARBOMER HOMOPOLYMER, UNSPECIFIED TYPE; GLYCERIN; TROLAMINE

LTD Global Trading 70% Alcohol Gel Hand Sanitizer

LTD Global Trading 70% Alcohol Gel Hand Sanitizer

Drug Facts

Active Ingredient(s)

Alcohol 70% v/v.

Purpose

Antiseptic

Use

Hand sanitizer to help reduce bacteria that potentially can cause disease. For use when soap and water are not available.

Warnings

Flammable. Keep away from source of heat, fire or flame.

For external use only.

Not for Consumption. Keep the product away from sunight.

When using this product avoid contact with eyes. If contact occurs, rinse thoroughly with water.

Stop use and ask a doctor if irritation or redness develops and lasts as these may be signs of a serious condition.

Keep out of reach of children. If swallowed, get medical help or contact a Poison Control Center right away.

Directions

- Place enough product in your palm to thoroughly cover your hands and rub hands together until dry.
- Children under 6 years should be supervised when using this product.

Storage

- Store at a temperature below 110°F (43°C)
- May discolor certain fabrics or surfaces

Inactive ingredients

Purified water, carbomer, glycerine, triethanolamine

Package Label - Principal Display Panel

NDC: 78072-400-

Made in Mexico